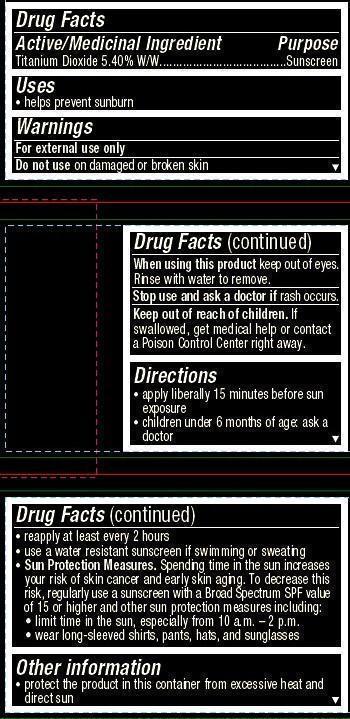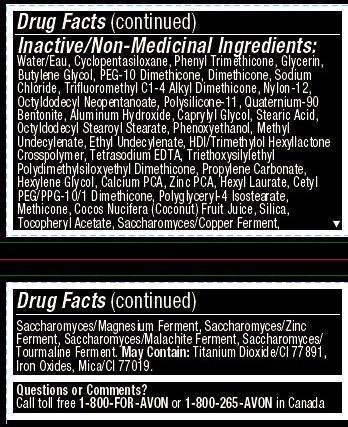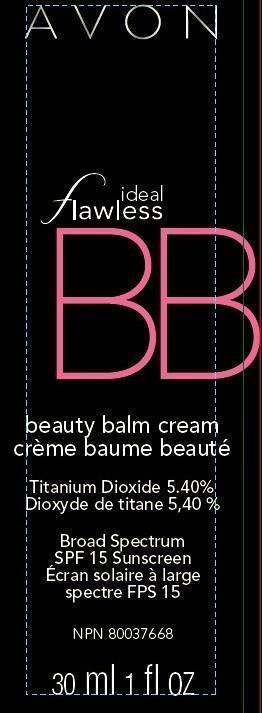 DRUG LABEL: Ideal Flawless
NDC: 10096-0293 | Form: CREAM
Manufacturer: New Avon LLC
Category: otc | Type: HUMAN OTC DRUG LABEL
Date: 20160217

ACTIVE INGREDIENTS: TITANIUM DIOXIDE 54 mg/1 mL

Active ingredient
Titanium Dioxide 5.40% W/W................................

Purpose
.................................Sunscreen

Uses
• helps prevent sunburn

Warnings
For external use only

Do not use on damaged or broken skin

When using this product keep out of eyes. Rinse with water to remove.

Stop use and ask a doctor if rash occurs

Keep out of reach of children. If swallowed, get medical help or contact a Poison Control Center right away.

Directions
• apply liberally 15 minutes before sun exposure
• children under 6 months of age: ask a doctor
• reapply at least every 2 hours
• use a water resistant sunscreen if swimming or sweating
• Sun Protection Measures. Spending time in the sun increases your risk of skin cancer and early skin aging. To decrease this risk, regularly use a sunscreen with a Broad Spectrum SPF value of 15 or higher and other sun protection measures including:
• limit time in the sun, especially from 10 a.m. – 2 p.m.
• wear long-sleeved shirts, pants, hats, and sunglasses

Other information

• protect the product in this container from excessive heat and direct sun

Inactive/Non-Medicinal Ingredients:
Water/Eau, Cyclopentasiloxane, Phenyl Trimethicone, Glycerin, Butylene Glycol, PEG-10 Dimethicone, Dimethicone, Sodium Chloride, Trifluoromethyl C1-4 Alkyl Dimethicone, Nylon-12, Octyldodecyl Neopentanoate, Polysilicone-11, Quaternium-90 Bentonite, Aluminum Hydroxide, Caprylyl Glycol, Stearic Acid, Octyldodecyl Stearoyl Stearate, Phenoxyethanol, Methyl Undecylenate, Ethyl Undecylenate, HDI/Trimethylol Hexyllactone Crosspolymer, Tetrasodium EDTA, Triethoxysilylethyl Polydimethylsiloxyethyl Dimethicone, Propylene Carbonate,
Hexylene Glycol, Calcium PCA, Zinc PCA, Hexyl Laurate, Cetyl PEG/PPG-10/1 Dimethicone, Polyglyceryl-4 Isostearate, Methicone, Cocos Nucifera (Coconut) Fruit Juice, Silica, Tocopheryl Acetate, Saccharomyces/Copper Ferment, Saccharomyces/Magnesium Ferment, Saccharomyces/Zinc Ferment, Saccharomyces/Malachite Ferment, Saccharomyces/Tourmaline Ferment. May Contain: Titanium Dioxide/CI 77891, Iron Oxides, Mica/CI 77019.

Questions or Comments?
Call toll free 1-800-FOR-AVON or 1-800-265-AVON in Canada